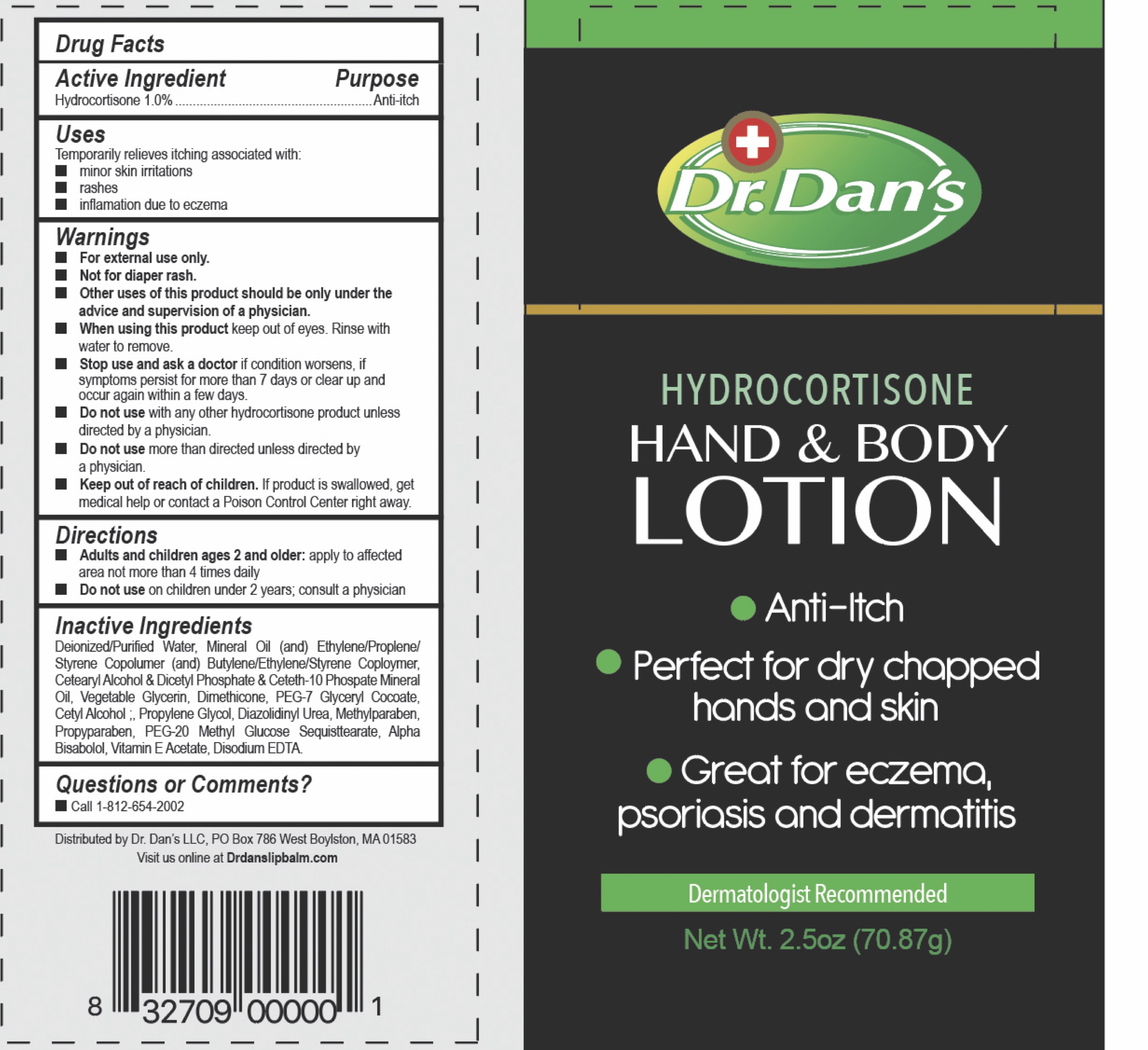 DRUG LABEL: HydrocortisoneLotion
NDC: 67516-0109 | Form: OINTMENT
Manufacturer: Dr. Dan's LLC
Category: otc | Type: HUMAN OTC DRUG LABEL
Date: 20191001

ACTIVE INGREDIENTS: HYDROCORTISONE 10 g/100 g
INACTIVE INGREDIENTS: MINERAL OIL; PETROLATUM; YELLOW WAX

Hydrocortisone Hand & Body Lotion

ACTIVE INGREDIENT

Hydrocortisone 1.0%

Inactive Ingredients: Beeswax, petroleum jelly, mineral oil.

Keep out of reach of children.